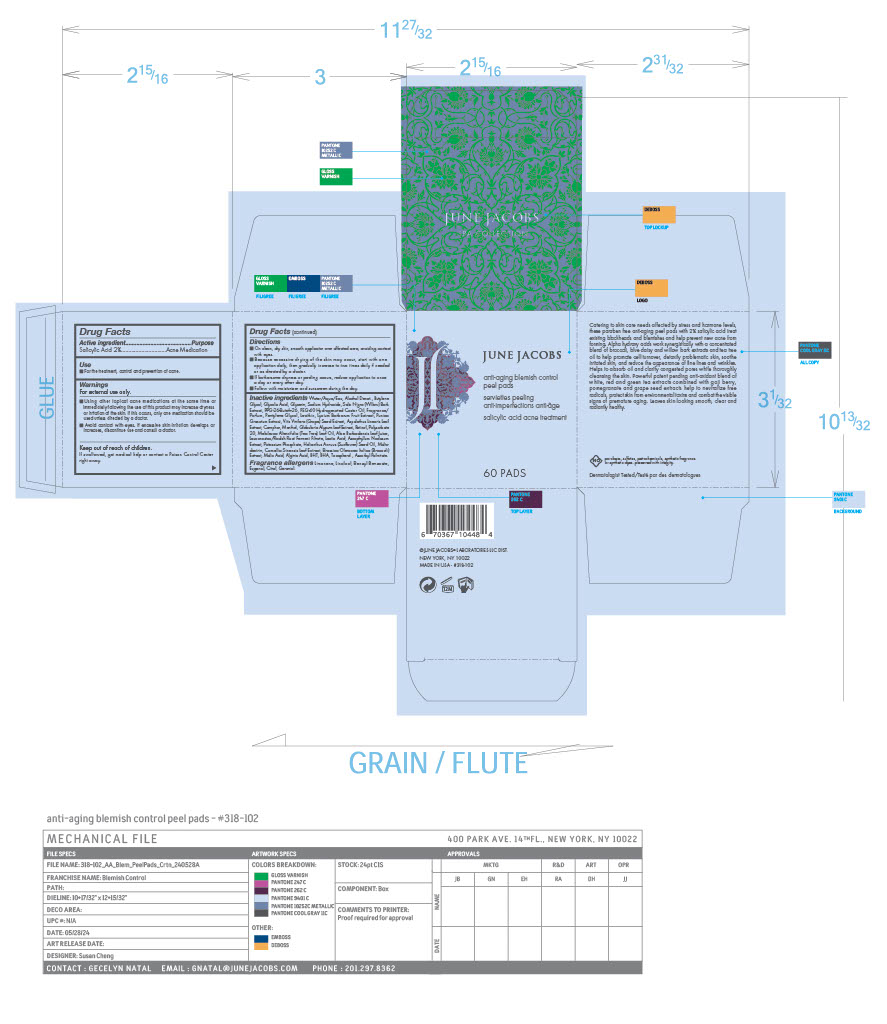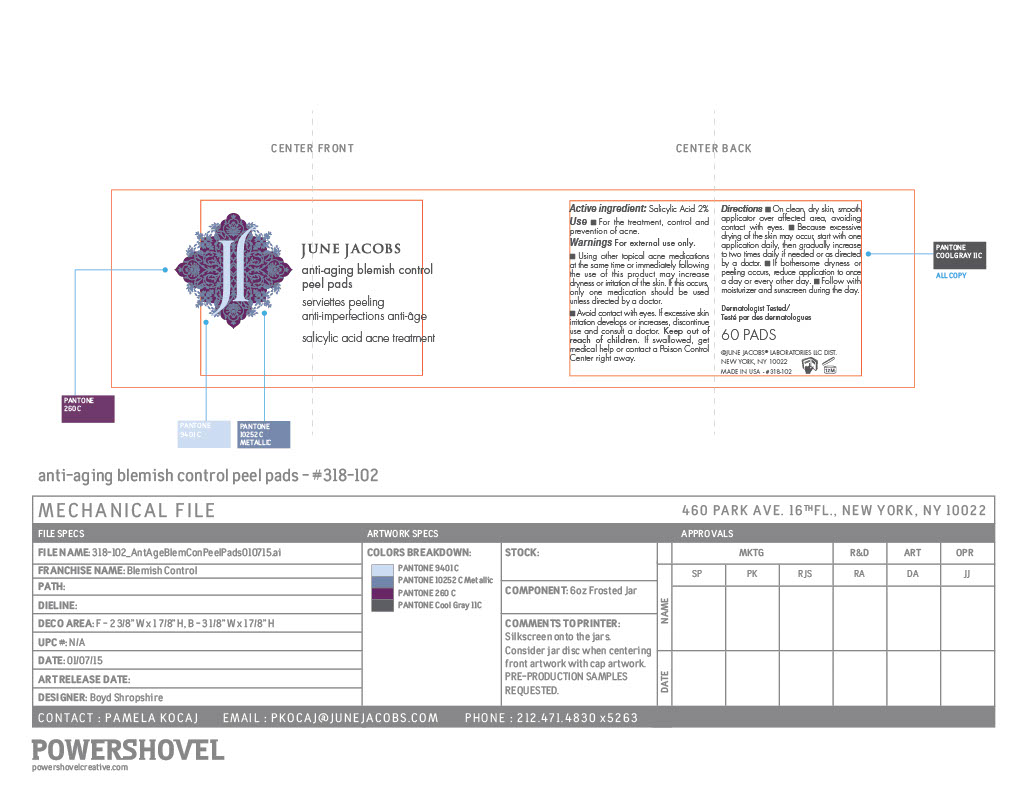 DRUG LABEL: Anti-Aging Blemish Control Peel Pads
NDC: 65278-318 | Form: SWAB
Manufacturer: June Jacobs Labs, LLC
Category: otc | Type: HUMAN OTC DRUG LABEL
Date: 20240521

ACTIVE INGREDIENTS: SALICYLIC ACID 2.366 g/118.29 g
INACTIVE INGREDIENTS: GLYCERIN; CARYOPHYLLENE; GLYCOLIC ACID; POLYOXYL 40 HYDROGENATED CASTOR OIL; GLOBULARIA CORDIFOLIA WHOLE; PENTYLENE GLYCOL; LECITHIN, SOYBEAN; MALTODEXTRIN; MALIC ACID; ASCOPHYLLUM NODOSUM; SUNFLOWER OIL; TOCOPHEROL; BENZYL BENZOATE; LEMON OIL; ORANGE OIL; CITRAL; GERANIOL; ASPALATHUS LINEARIS LEAF; 3-HEXEN-1-OL, (3Z)-; SODIUM HYDROXIDE; SALIX NIGRA BARK; CLOVE LEAF OIL; VITIS VINIFERA SEED; ASCORBYL PALMITATE; MELALEUCA ALTERNIFOLIA (TEA TREE) LEAF OIL; ALGINIC ACID; LIMONENE, (+)-; ALCOHOL; MANDARIN OIL; LINALYL ACETATE; POLYSORBATE 20; POTASSIUM PHOSPHATE, UNSPECIFIED FORM; BROCCOLI SPROUT; LYCIUM BARBARUM FRUIT; BUTYLENE GLYCOL; CITRONELLA OIL; RETINOL; GREEN TEA LEAF; BUTYLATED HYDROXYTOLUENE; WATER; PPG-26-BUTETH-26; GINGER OIL; LINALOOL, (+/-)-; MENTHOL; ALOE VERA LEAF; LACTIC ACID; PUNICA GRANATUM ROOT BARK; CAMPHOR (SYNTHETIC); LEUCONOSTOC/RADISH ROOT FERMENT FILTRATE; BUTYLATED HYDROXYANISOLE

Anti-Aging Blemish Control Peel Pads

Active ingredients

Salicylic Acid 2%

PURPOSE

Acne Medication

Use

■ For the treatment, control and prevention of acne.

Warnings

For external use only.

WHEN USING

■ Using other topical acne medications at the same time or immediately following the use of this product may increase dryness or irritation of the skin. If this occurs, only one medication should be used unless directed by a doctor.

■ Avoid contact with eyes.

STOP USE

If excessive skin irritation develops or increases, discontinue use and consult a doctor.

Keep out of reach of children. If swallowed, get medical help or contact a Poison Control Center right away.

Directions

■ On clean, dry skin, smooth applicator over affected area, avoiding contact with eyes

■ Because excessive drying of the skin may occur, start with one application daily, then gradually increase to two times daily if needed or as directed by a doctor.

■ If bothersome dryness or peeling occurs, reduce application to once a day or every other day.

■ Follow with moisturizer and sunscreen during the day.

Inactive ingredients

Water/Aqua/Eau, Alcohol Denat., Butylene Glycol, Glycolic Acid, Glycerin, Sodium Hydroxide, Salix Nigra (Willow) Bark Extract, PPG-26-Buteth-26, PEG-40 Hydrogenated Castor Oil, Fragrance/ Parfum, Pentylene Glycol, Lecithin, Lycium Barbarum Fruit Extract, Punica Granatum Extract, Vitis Vinifera (Grape) Seed Extract, Aspalathus Linearis Leaf Extract, Camphor, Menthol, Globularia Alypum Leaf Extract, Retinol, Polysorbate 20, Melaleuca Alternifolia (Tea Tree) Leaf Oil, Aloe Barbadensis Leaf Juice, Leuconostoc/Radish Root Ferment Filtrate, Lactic Acid, Ascophyllum Nodosum Extract, Potassium Phosphate, Helianthus Annuus (Sunflower) Seed Oil, Malto dextrin, Camellia Sinensis Leaf Extract, Brassica Oleracea Italica (Broccoli) Extract, Malic Acid, Alginic Acid, BHT, BHA, Tocopherol , Ascorbyl Palmitate, Limonene, Linalool, Benzyl Benzoate, Eugenol, Citral, Geraniol